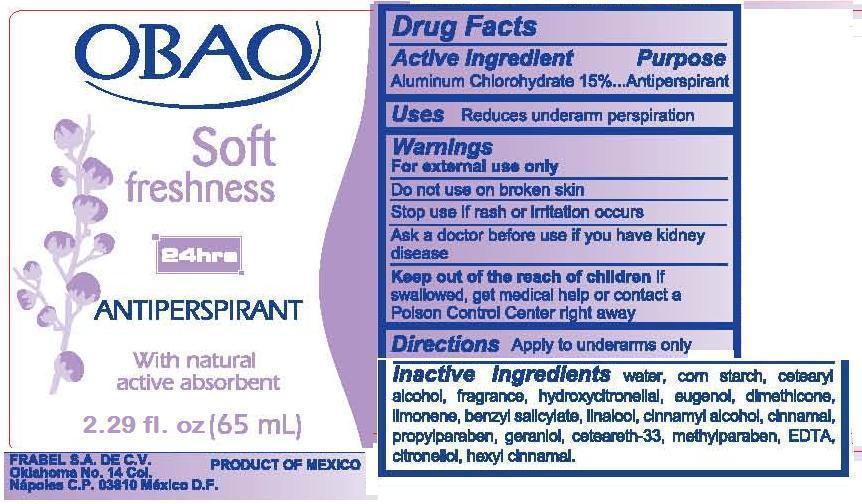 DRUG LABEL: OBAO
NDC: 51769-105 | Form: LIQUID
Manufacturer: ALL NATURAL DYNAMICS
Category: otc | Type: HUMAN OTC DRUG LABEL
Date: 20130902

ACTIVE INGREDIENTS: ALUMINUM CHLOROHYDRATE 15 g/100 g
INACTIVE INGREDIENTS: WATER; STARCH, CORN; CETOSTEARYL ALCOHOL; EUGENOL; DIMETHICONE; LIMONENE, (+)-; BENZYL SALICYLATE; LINALOOL, DL-; CINNAMYL ALCOHOL; PROPYLPARABEN; GERANIOL; METHYLPARABEN; EDETIC ACID; .BETA.-CITRONELLOL, (+/-)-

Active Ingredients

Aluminum chlorohydrate 15%

Purpose

Antiperspirant

Uses

Reduces underarm perspiration

Warnings

For external use only

Do not use on broken skin.

Stop use if rash or irritation occurs.

Ask a doctor before use if you have kidney disease

PREGNANCY OR BREAST FEEDING

If pregnant or breast-feeding, ask a health professional before use.

Keep out of reach of children. If swallowed get medical help or contact a Poison Control Center right away.

Directions

Apply to underarms only

Inactive Ingredients

water, corn starch, cetearyl alcohol, fragrance, hydroxycitronellal, eugenol, dimethicone, limonene, benzyl salcylate, linalool, cinnamyl alcohol, cinnamal,
propylparaben, geraniol, ceteareth-33, methylparaben, EDTA, citronellol, hexyl cinnamal